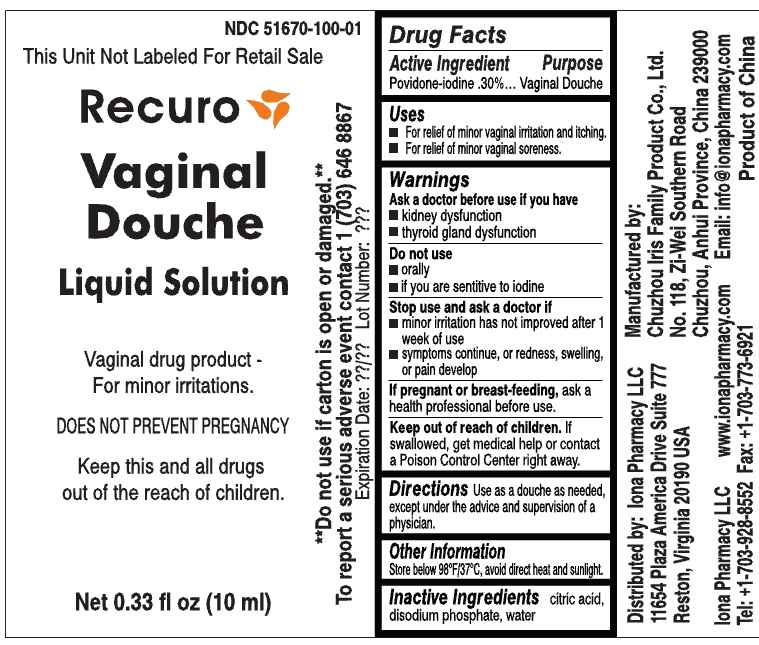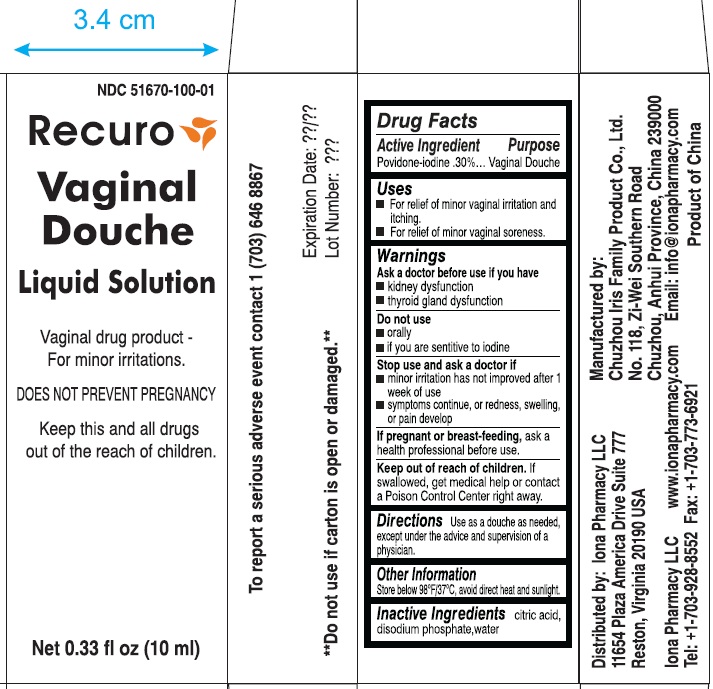 DRUG LABEL: RECURO VAGINAL 
NDC: 51670-100 | Form: DOUCHE
Manufacturer: IONA PHARMACY
Category: otc | Type: HUMAN OTC DRUG LABEL
Date: 20101025

ACTIVE INGREDIENTS: POVIDONE-IODINE 0.30 mL/100 mL
INACTIVE INGREDIENTS: CITRIC ACID MONOHYDRATE; PHOSPHATE ION; WATER

RECURO VAGINAL DOUCHE LIQUID SOLUTION

Drug Facts

Active Ingredient Purpose

Povidone-Iodine 0.30%..............Vaginal Douche

Purpose

Vaginal Douche

Uses

For relief of minor vaginal irritation and itching

For relief of minor vaginal soreness.

Warnings

Ask a doctor before use if you have

Kidney disfunction

Thyroid gland dysfunction

Do not use

orally

if you are sensitive to iodine

Stop use and ask a doctor if

minor irritation has not improved after 1 week of use

symptoms continue or redness, swelling or pain develop

PREGNANCY OR BREAST FEEDING

If pregnant or breasts feeding, ask a health professional before use.

Keep out of reach of children. If swallowed, get medical help or contact a Poison control center right away.

DOSAGE AND ADMINISTRATION

Directions. Use as a douche as needed, except under the advice and supervision of a physician.

Other Information

Store below 98F/37C avoid direct heat and sunlight

Inactive Ingredients
citric acid, disodium phosphate, water

PACKAGE LABEL

NDC 51670-100-01

This unit not relabeled for retail sale.

Recuro

Vaginal Douche

Liquid Solution

Vaginal Drug Product- For minor irritations

DOES NOT PREVENT PREGNANCY

keep this and all drugs out of the reach of children.

net 0.33 fl oz (10ml)

**do not use if carton is open or damaged.**

To report a serious adverse event contact 1 (703) 646-8867

Expiration date Lot Number

Distributed by Iona Pharmacy LLC

11654 Plaza America Drive Suite 777

Reston, Virginia 20190 USA

Iona Pharmacy LLC

www.iona pharmacy .com

Tel: +1-703-928-8552 Fax: 1-703-773-6921

Manufactured by:

Chuzhou Iris Family Product Co., Ltd.

No. 118, Ze-Wei Southern Road

Chuzhou, Anhui Province, China 239000

Email: info@ionapharmacy.com

Product of China